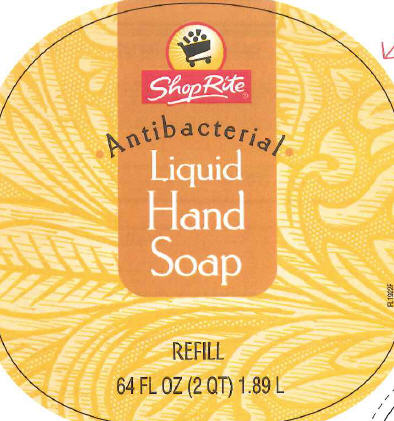 DRUG LABEL: Antibacterial Hand
NDC: 41190-243 | Form: LIQUID
Manufacturer: Wakefern Food Corporation
Category: otc | Type: HUMAN OTC DRUG LABEL
Date: 20120601

ACTIVE INGREDIENTS: TRICLOSAN 0.15 kg/100 L
INACTIVE INGREDIENTS: WATER; SODIUM LAURETH SULFATE; SODIUM LAURYL SULFATE; COCAMIDOPROPYL BETAINE; SODIUM CHLORIDE; DECYL GLUCOSIDE; GLYCERIN; PEG-18 GLYCERYL OLEATE/COCOATE; COCO MONOETHANOLAMIDE; DMDM HYDANTOIN; EDETATE SODIUM; CITRIC ACID MONOHYDRATE; FD&C YELLOW NO. 5; FD&C RED NO. 4

Drug Facts

ShopRite Antibacterial Liquid Hand Soap is made with an antibacterial formula that eliminates the dirt yo see and the germs you don't. ShopRite Antibacterial Liquid Hand Soap actually helps kill
germs and bacteria on contact so its perfect for use at both bathroom and kitchen sink. ShopRite Antibacterial Liquid Hand Soap is effective, yet gentle and mild, so it's great for the entire family.

Active Ingredient
Triclosan 0.15%

Purpose
Antibacterial

INDICATIONS AND USAGE

Uses for handwashing to decrease bacteria on the skin

Warnings
For external use only.

When using this product •do not get into eyes. If contact occurs rinse eyes thoroughly with water.

Stop use and ask a doctor if •irritation or redness develops.

Keep out of reach of children. If swallowed, get medical help or contact a Poison Control Center right away.

DOSAGE AND ADMINISTRATION

Directions • wet hands •apply palmful to hands •scrub thoroughly •rinse

INACTIVE INGREDIENT

Inactive ingredients water, sodium laureth sulfate, sodium, lauryl sulfate, cocamidopropyl betaine, sodium chloride, decyl glucoside, glycerin,
PEG-18 glyceryl oleate/cocoate, fragrance, cocamide MEA, DMDM hydantoin, tetrasodium EDTA, citric acid, yellow 5, red 4

ADVERSE REACTIONS

Quality Guarantee
We welcome your questions and comments.
Call: 1-800-ShopRite (8am-8pm EST)
E-mail: www.shoprite.com
Write: Wakefern Food Corp. Consumer Affairs P7-103
600 York St Elizabeth, NJ07207
Please provide product UPC and code stamped on product
Distributed by Wakefern Food Corporation
5000 Riverside Drive
Keasbey, NJ 08832

PACKAGE LABEL

ShopRite
Antibacterial
Liquid
Hand
Soap
Refill
64 FL OZ (2QT) 1.89 L